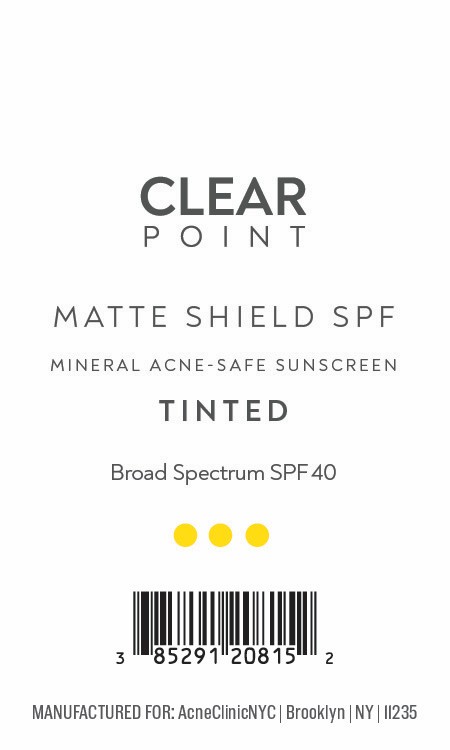 DRUG LABEL: MATTE SHIELD SPF
NDC: 85291-208 | Form: CREAM
Manufacturer: ACNE SOLUTIONS NYC INC
Category: otc | Type: HUMAN OTC DRUG LABEL
Date: 20251208

ACTIVE INGREDIENTS: ZINC OXIDE 160 mg/1 g
INACTIVE INGREDIENTS: PEG-10 DIMETHICONE (600 CST); POLYHYDROXYSTEARIC ACID (2300 MW); HYDROGEN DIMETHICONE (20 CST); DIMETHICONE; DIMETHICONE/VINYL DIMETHICONE CROSSPOLYMER (SOFT PARTICLE); CYCLOPENTASILOXANE; CAPRYLIC/CAPRIC TRIGLYCERIDE; CERAMIDE 3; CYCLOHEXASILOXANE; DIMETHICONE CROSSPOLYMER; VINYL DIMETHICONE/METHICONE SILSESQUIOXANE CROSSPOLYMER; ALPHA-TOCOPHEROL ACETATE; DIMETHICONOL (2000 CST); TETRAHEXYLDECYL ASCORBATE; CI 77499; CI 77491; CI 77492

Active Ingredient:

Zinc Oxide 16%

Purpose:

Sunscreen

Warning:

For external use only. Keep out of the reach of children.

Warning:

For external use only. Keep out of reach of children.

Directions:

Apply liberally 15 minutes before sun exposure.

INACTIVE INGREDIENT

Capric/Caprylic Triglyceride, Ceramide 3, Cyclohexasiloxane, Cyclopentasiloxane, Dimethicone, Dimethicone Crosspolymer, Dimethicone/Vinyl Dimethicone Crosspolymer, Dimethiconol, Iron Oxide, Hydrogen Dimethicone, PEG-10 Dimethicone, Polyhydroxystearic Acid, Tetrahexyldecyl Ascorbate, Tocopheryl Acetate, Vinyl Dimethicone/Methicone Silsesquioxane Crosspolymer

OTHER SAFETY INFORMATION

SAMPLE NOT FOR RESALE

Warning:

Keep out of reach of children